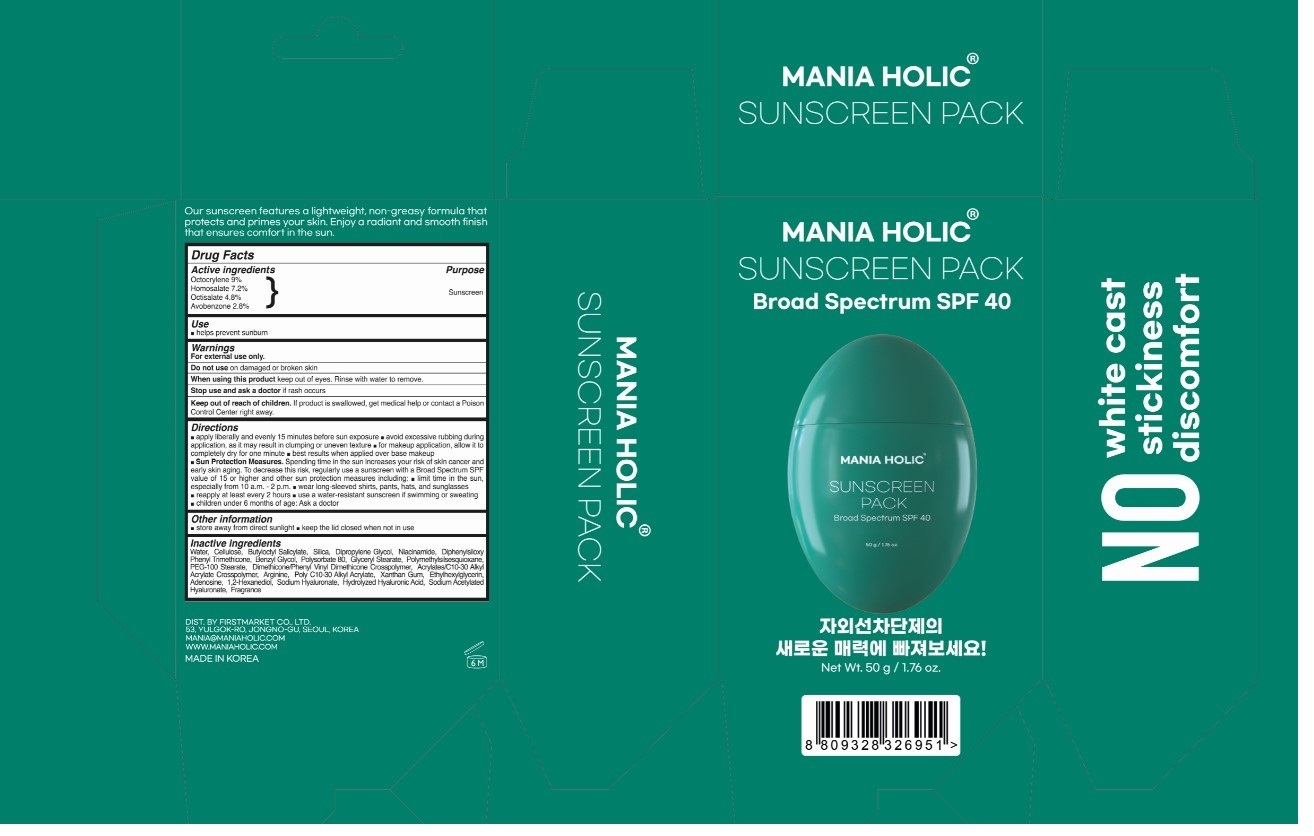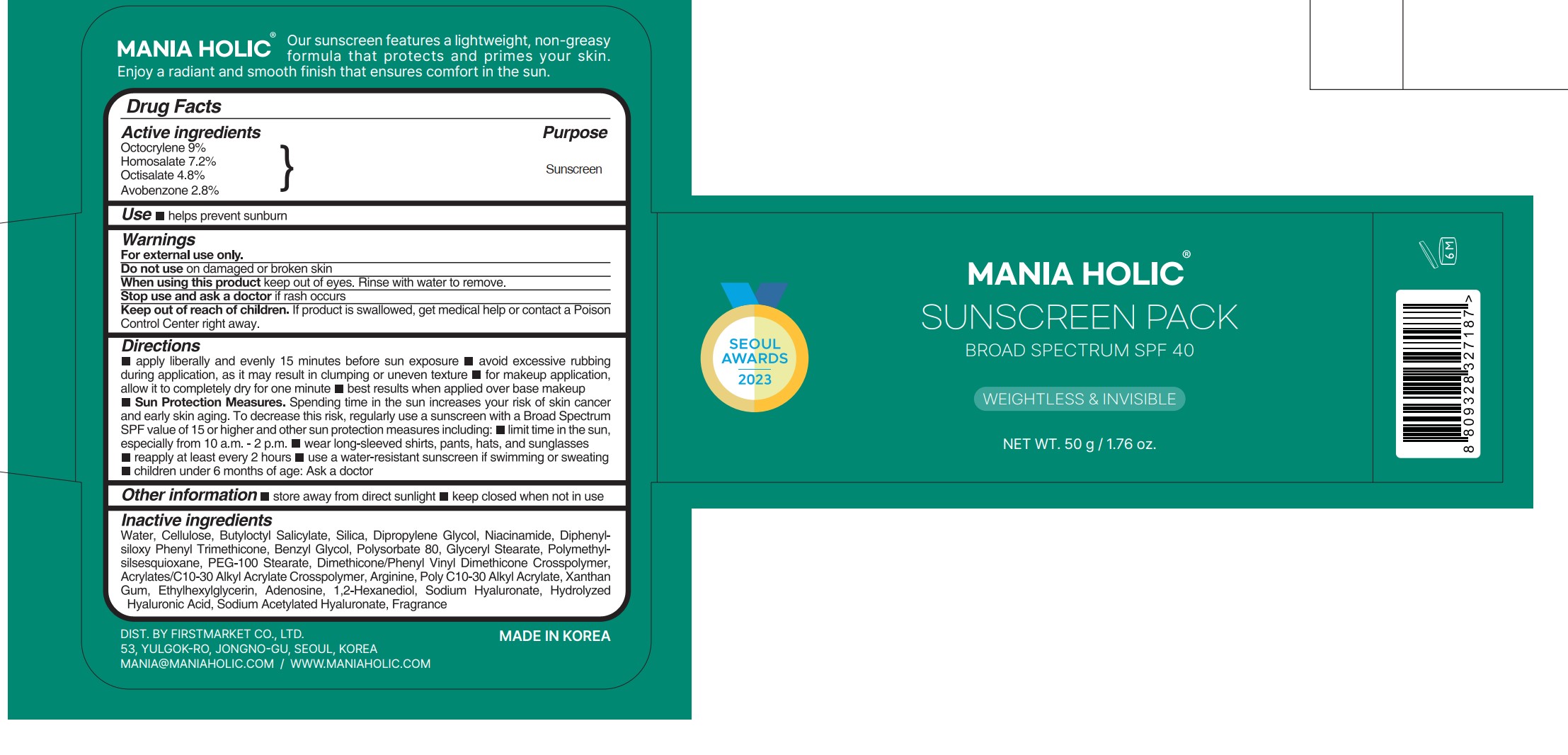 DRUG LABEL: Mania Holic Sunscreen Pack
NDC: 83888-001 | Form: CREAM
Manufacturer: Firstmarket Co., ltd.
Category: otc | Type: HUMAN OTC DRUG LABEL
Date: 20260123

ACTIVE INGREDIENTS: OCTOCRYLENE 90 mg/1 g; HOMOSALATE 72 mg/1 g; OCTISALATE 48 mg/1 g; AVOBENZONE 28 mg/1 g
INACTIVE INGREDIENTS: WATER; POWDERED CELLULOSE; BUTYLOCTYL SALICYLATE; SILICON DIOXIDE; DIPROPYLENE GLYCOL; NIACINAMIDE; DIPHENYLSILOXY PHENYL TRIMETHICONE; ETHYLENE GLYCOL MONOBENZYL ETHER; POLYSORBATE 80; GLYCERYL MONOSTEARATE; POLYMETHYLSILSESQUIOXANE (4.5 MICRONS); PEG-100 STEARATE; DIMETHICONE/PHENYL VINYL DIMETHICONE CROSSPOLYMER; ACRYLATES/C10-30 ALKYL ACRYLATE CROSSPOLYMER (60000 MPA.S); ARGININE; BEHENYL ACRYLATE POLYMER; XANTHAN GUM; ETHYLHEXYLGLYCERIN; ADENOSINE; 1,2-HEXANEDIOL; HYALURONATE SODIUM; SODIUM ACETYLATED HYALURONATE

83888-001_Mania Holic Sunscreen Pack

DOSAGE AND ADMINISTRATION

Apply liberally 15 minutes before sun exposure. avoid excessive rubbing during application, as it may result in clumping or uneven texture, for makeup application, allow it to completely dry for one minute, best results when applied over base makeup.
Sun protection measures. Spending time in the sun increases your risk of skin cancer and early skin aging. To decrease this risk, regularly use a sunscreen with a broad spectrum SPF of 15 of higher and other sun protection measures including: Limited time in the sun, especially from 10 am to 2 pm, Wear long-sleeve shirts, pants, hats, and sunglasses. reapply at least every 2 hours, use a water-resistant sunscreen if swimming or sweating.
Children under 6 months of age: Ask a doctor

ACTIVE INGREDIENT

Octocrylene 9%

Homosalate 7.2%

Octisalate 4.8%

Avobenzone 2.8%

PURPOSE

Sunscreen

INDICATIONS AND USAGE

Helps prevent sunburn

WARNINGS

For external use only

Do not use on damaged or broken skin

When using this product, keep out of eyes. Rinse with water to remove.

Stop using and ask a doctor if rash occurs.

KEEP OUT OF REACH OF CHILDREN

Keep out of reach of the children. If product is swallowed, get medical help or contact a poison control center right away.

INACTIVE INGREDIENT

Water, Cellulose, Butyloctyl Salicylate, Silica, Dipropylene Glycol, Niacinamide, Diphenylsiloxy Phenyl Trimethicone, Benzyl Glycol, Polysorbate 80, Glyceryl Stearate, Polymethylsilsesquioxane, PEG-100 Stearate, Dimethicone/Phenyl Vinyl Dimethicone Crosspolymer, Acrylates/C10-30 Alkyl Acrylate Crosspolymer, Arginine, Poly C10-30 Alkyl Acrylate, Xanthan Gum, Ethylhexylglycerin, Adenosine, 1,2-Hexanediol, Sodium Hyaluronate, Hydrolyzed Hyaluronic Acid, Sodium Acetylated Hyaluronate, Fragrance

OTHER SAFETY INFORMATION

Store away from direct sunlight.

Keep the lid closed when not in use.